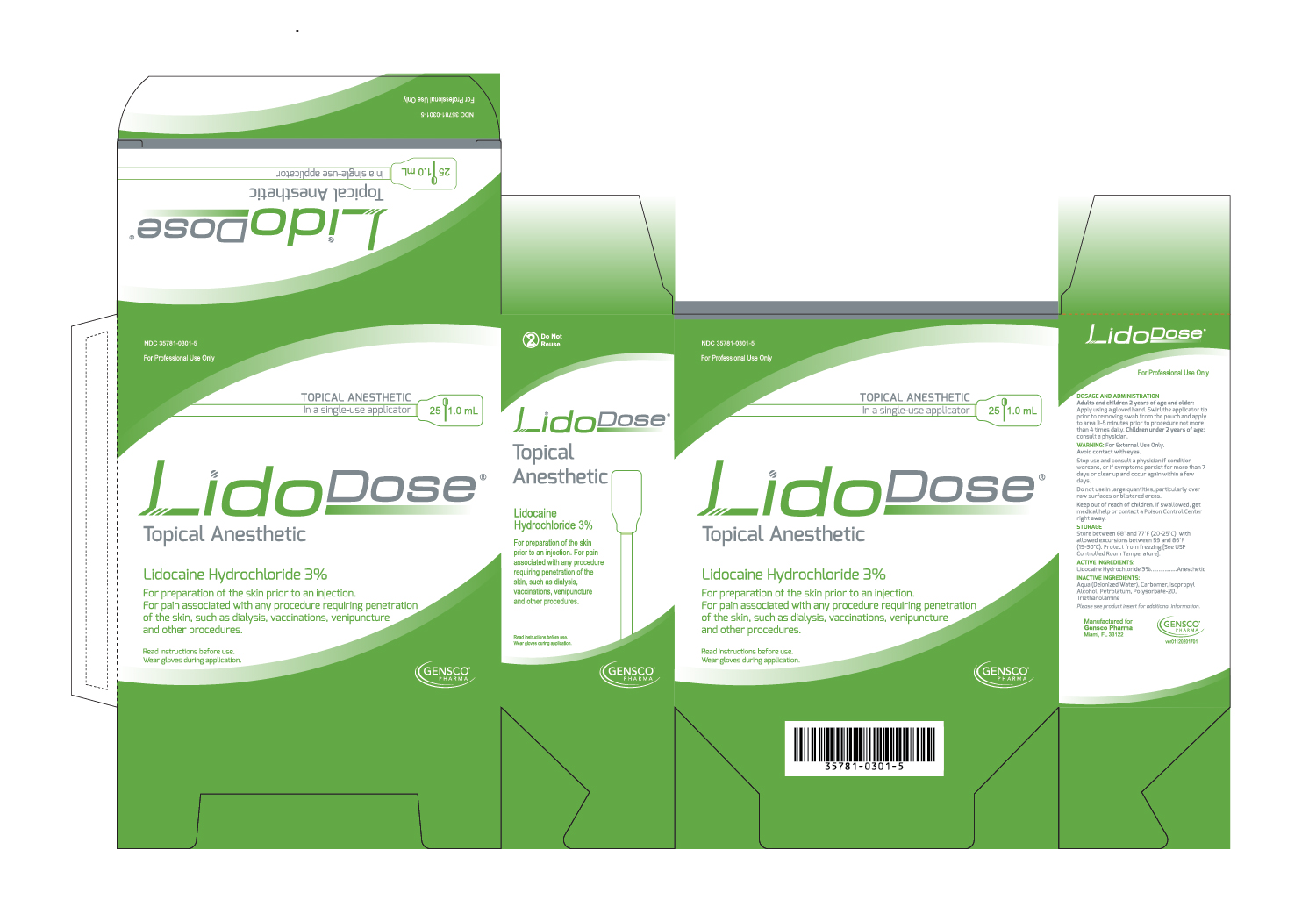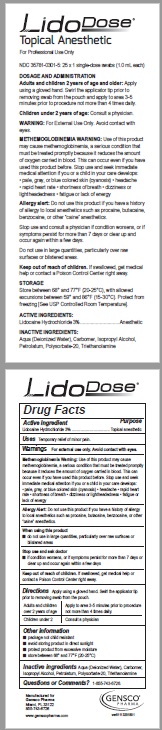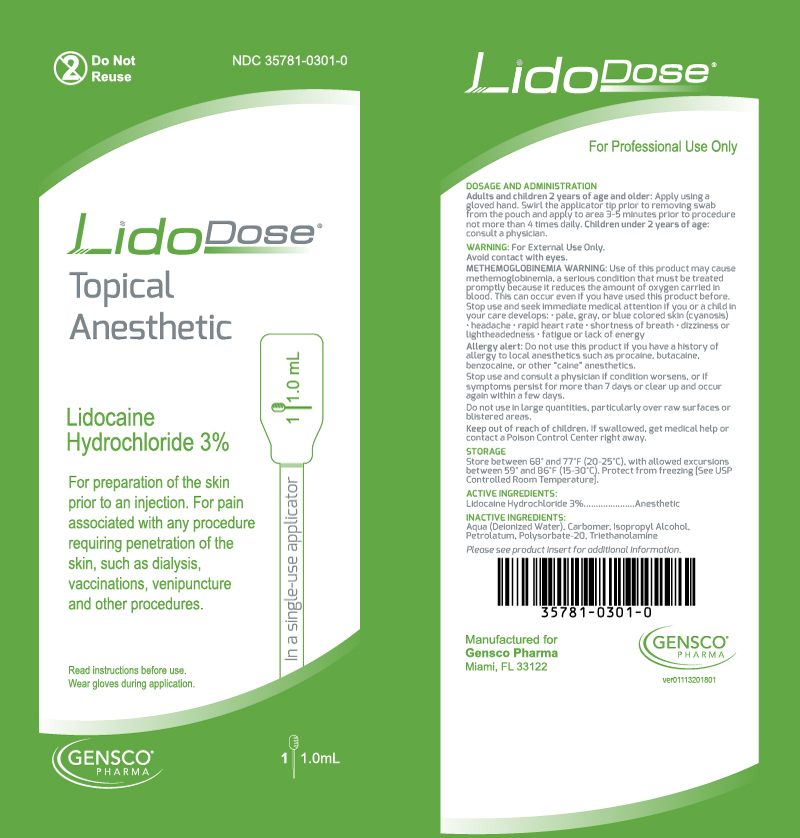 DRUG LABEL: Lidodose
NDC: 35781-0301 | Form: GEL
Manufacturer: Gensco Laboratories, LLC
Category: otc | Type: HUMAN OTC DRUG LABEL
Date: 20221004

ACTIVE INGREDIENTS: LIDOCAINE HYDROCHLORIDE 3 mg/100 mL
INACTIVE INGREDIENTS: WATER; CARBOMER HOMOPOLYMER TYPE C (ALLYL PENTAERYTHRITOL CROSSLINKED); ISOPROPYL ALCOHOL; PETROLATUM; POLYSORBATE 20; TRIETHANANOLAMINE PHENYLBENZIMIDAZOLE SULFONATE

LidoDose Topical Anesthetic

Dosage and Administration

Adults and children 2 years of age and older: Apply using a gloved hand. Swirl the applicator tip prior to removing swab from the pouch and apply to area 3-5 minutes prior to procedure not more than 4 times daily.

Children under 2 years of age: consult a physician.

Usage

Pain relief

Warning: for external use only.

Methemoglobinemia

Cases of methemoglobinemia have been reported in association with local anesthetic use. Although all patients are at risk for methemoglobinemia, patients with glucose-6-phosphate dehydrogenase deficiency, congenital or idiopathic methemoglobinemia, cardiac or pulmonary compromise, infants under 6 months of age, and concurrent exposure to oxidizing agents or their metabolites are more susceptible to developing clinical manifestations of the condition. If local anesthetics must be used in these patients, close monitoring for symptoms and signs of methemoglobinemia is recommended.

Signs and symptoms of methemoglobinemia may occur immediately or may be delayed some hours after exposure and are characterized by a cyanotic skin discoloration and abnormal coloration of the blood. Methemoglobin levels may continue to rise; therefore, immediate treatment is required to avert more serious central nervous system and cardiovascular adverse effects, including seizures, coma, arrhythmias, and death. Discontinue LidoDose and any other oxidizing agents. Depending on the severity of the symptoms, patients may respond to supportive care, i.e., oxygen therapy, hydration. More severe symptoms may require treatment with methylene blue, exchange transfusion, or hyperbaric oxygen.

Avoid contact with eyes.

Stop use and consult a physician if condition worsens, or if symptoms persist for more than 7 days or clear up and occur again within a few days. Do not use in large quantities, particularly over raw surfaces or blistered areas.

DRUG INTERACTIONS

Patients that are administered local anesthetics may be at increased risk of developing methemoglobinemia when concurrently exposed to the following oxidizing agents:

Class | Examples
Nitrates/Nitrites | nitroglycerin, nitroprusside, nitric oxide, nitrous oxide
Local anesthetics | benzocaine, lidocaine, bupivacaine, inepivacaine, tetracaine, prilocaine, procaine, articaine, ropivacaine
Antineoplastic agents | cyclophosphamide, flutamide, rasburicase, ifosfamide, hydroxyurea
Antibiotics | dapsone, sulfonamides, nitrofurantoin, para¬aminosalicylic acid
Antimalarials | chloroquine, primaquine
Anticonvulsants | phenytoin, sodium valproate, phenobarbital
Other drugs | acetaminophen, metoclopramide, sulfa drugs (i.e., sulfasalazine), quinine

Keep out of reach of children

If swallowed, get medical help or contact a Poison Control Center right away.

Storage

Store between 68 and 77 F (20 - 25 C), with allowed excursions between 59 and 86 F (15 - 30 C). Protect from freezing. (See USP Controlled Room Temperature).

PATIENT COUNSELING INFORMATION

Inform patients that use of local anesthetics may cause methemoglobinemia, a serious condition that must be treated promptly. Advise patients or caregivers to stop use and seek immediate medical attention if they or someone in their care experience the following signs or symptoms: pale, gray, or blue colored skin (cyanosis); headache; rapid heart rate; shortness of breath; lightheadedness; or fatigue.

Active Ingredients:

Lidocaine Hydrochloride 3%

Purpose:

Anesthetic

Inactive Ingredients:

Aqua (Deionized Water), Carbomer, Isopropyl Alcohol, Petrolatum, Polysorbate-20, Triethanolamine

Please see product insert for additional information.